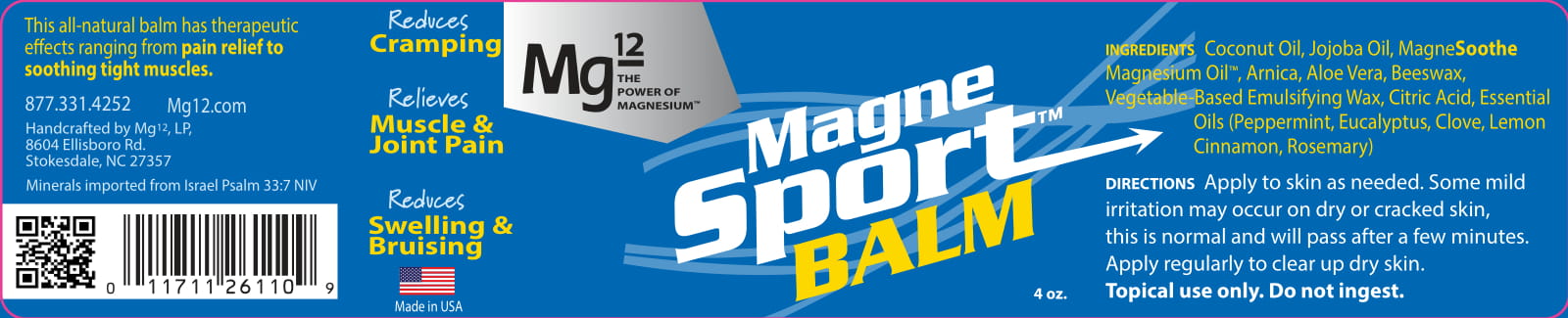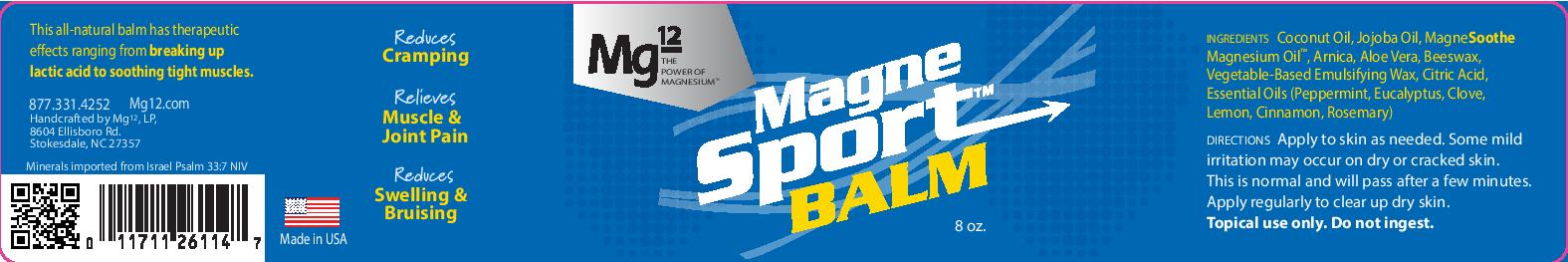 DRUG LABEL: MagneSoothe Body Balm
NDC: 78735-2000 | Form: SALVE
Manufacturer: Mg12, LP
Category: otc | Type: HUMAN OTC DRUG LABEL
Date: 20201018

ACTIVE INGREDIENTS: ISOPROPYL ALCOHOL 0.25 mL/120 mL
INACTIVE INGREDIENTS: JOJOBA OIL 25 mL/120 mL; PEG-8 BEESWAX 10.82 mL/120 mL; CITRIC ACID ACETATE 0.1 mL/120 mL; ALOE VERA LEAF 7 mL/120 mL; GLYCERYL STEARATE SE 11 mL/120 mL; MAGNESIUM CHLORIDE 27 mL/120 mL; COCONUT OIL 32 mL/120 mL; LAVENDER OIL 0.01 mL/120 mL

MagneSport Body Balm

Purpose

To provide muscle relief.

Hazards/Warnings

Description of necessary first-aid measures

If inhaled Do NOT induce vomiting. Never give anything by mouth to an unconscious person.

Rinse mouth with water. Consult a physician.

In case of skin contact N/A
In case of eye contact Flush eyes with water as a precaution.
If swallowed Rinse mouth. If vomiting occurs naturally, have victim lean forward to reduce the risk
of aspiration. Do NOT induce vomiting unless directed to do so by
medical personnel. Never give anything by mouth to an unconscious
person. Call a poison center or doctor if you feel unwell.
Acute and delayed symptoms and effects: Harmful if swallowed. May cause gastrointestinal
irritation. Signs/symptoms may include abdominal pain, stomach
upset, nausea, vomiting and diarrhea.

Hazard identification

Classification of the substance or mixture
GHS classification in accordance with: OSHA (29 CFR 1910.1200)
GHS label elements, including precautionary statements

DOSAGE AND ADMINISTRATION

1. Coconut oil
Concentration Not specified
EC no. 232-282-8
CAS no. 8001-31-8

2. Yellow Beeswax
Concentration Not specified

3. Emulsifying Wax
Concentration Not specified

4. Jojoba oil glycereth-8 esters

Concentration Not specified

5. Magnesium chloride
Concentration Not specified
EC no. 232-094-6
CAS no. 7786-30-3

6. Magnesium oil
Concentration Not specified

7. Aloe vera callus extract
Concentration Not specified

8. Citric acid
Concentration Not specified
EC no. 201-069-1
CAS no. 77-92-9
- Eye damage/irritation, Cat. 2A

9. Lavandula angustifolia extract
Concentration Not specified
CAS no. 90063-37-9

10. Water
Concentration Not specified
EC no. 231-791-2
CAS no. 7732-18-5

INACTIVE INGREDIENT

1. Coconut oil
Concentration Not specified
EC no. 232-282-8
CAS no. 8001-31-8
2. Yellow Beeswax
Concentration Not specified
3. Emulsifying Wax
Concentration Not specified
4. Jojoba oil glycereth-8 esters

Concentration Not specified
5. Magnesium chloride
Concentration Not specified
EC no. 232-094-6
CAS no. 7786-30-3
6. Magnesium oil
Concentration Not specified
7. Aloe vera callus extract
Concentration Not specified
8. Citric acid
Concentration Not specified
EC no. 201-069-1
CAS no. 77-92-9
- Eye damage/irritation, Cat. 2A
9. Lavandula angustifolia extract
Concentration Not specified
CAS no. 90063-37-9
10. Water
Concentration Not specified
EC no. 231-791-2
CAS no. 7732-18-5

ACTIVE INGREDIENT

Isopropyl Alcohol .25 ml per 100 ml

Keep out of reach of children. In case of overdose, get medical help or contact a Poison Control Center right away.

Overdoses may cause diahrrea

Usage

Apply generously on affected areas.

PACKAGE LABEL

500 gram bottle MagneSport Body Balm